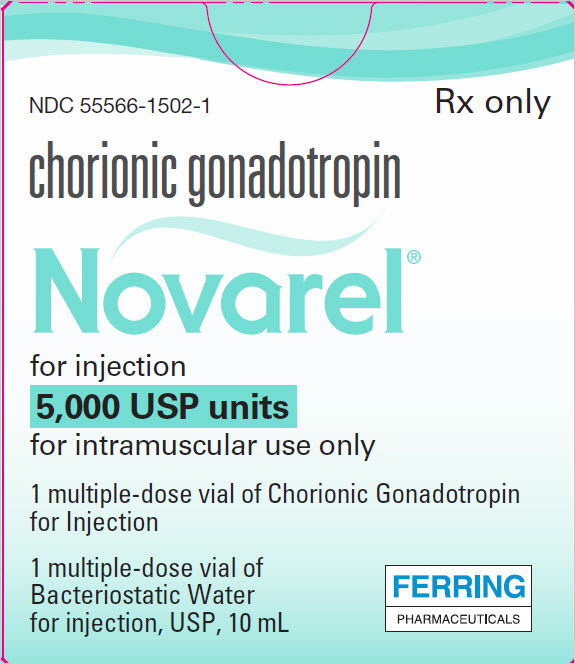 DRUG LABEL: Novarel
NDC: 55566-1502 | Form: KIT | Route: INTRAMUSCULAR
Manufacturer: Ferring Pharmaceuticals Inc.
Category: prescription | Type: HUMAN PRESCRIPTION DRUG LABEL
Date: 20250827

ACTIVE INGREDIENTS: CHORIONIC GONADOTROPIN 5000 [USP'U]/1 1
INACTIVE INGREDIENTS: MANNITOL; SODIUM PHOSPHATE, DIBASIC, UNSPECIFIED FORM; SODIUM PHOSPHATE, MONOBASIC, UNSPECIFIED FORM; WATER

NOVAREL® (chorionic gonadotropin) for injection, for intramuscular use
Initial U.S. Approval: 1974

Rx Only

DESCRIPTION

Human chorionic gonadotropin (HCG), a polypeptide hormone produced by the human placenta, is composed of an alpha and a beta subunit. The alpha subunit is essentially identical to the alpha subunits of the human pituitary gonadotropins, luteinizing hormone (LH) and follicle-stimulating hormone (FSH), as well as to the alpha subunit of human thyroid-stimulating hormone (TSH). The beta subunits of these hormones differ in amino acid sequence.

NOVAREL (chorionic gonadotropin) for injection is a water soluble glycoprotein derived from human pregnancy urine and administered intramuscularly after reconstitution. The sterile lyophilized powder is stable. When reconstituted with Bacteriostatic Water for Injection preserved with benzyl alcohol 0.9%, the solution should be refrigerated and used within 30 days.

Each 5,000 USP units vial contains:

chorionic gonadotropin 5,000 USP Units, Dibasic Sodium Phosphate 16 mg, Mannitol 100 mg, and Monobasic Sodium Phosphate 4 mg.

Each 10,000 USP units vial contains:

chorionic gonadotropin 10,000 USP Units, Dibasic Sodium Phosphate 16 mg, Mannitol 100 mg, and Monobasic Sodium Phosphate 4 mg.

CLINICAL PHARMACOLOGY

The action of HCG is virtually identical to that of pituitary LH, although HCG appears to have a small degree of FSH activity as well. It stimulates production of gonadal steroid hormones by stimulating the interstitial cells (Leydig cells) of the testis to produce androgens and the corpus luteum of the ovary to produce progesterone. Androgen stimulation in the male leads to the development of secondary sex characteristics and may stimulate testicular descent when no anatomical impediment to descent is present. This descent is usually reversible when HCG is discontinued. During the normal menstrual cycle, LH participates with FSH in the development and maturation of the normal ovarian follicle, and the mid-cycle LH surge triggers ovulation. HCG can substitute for LH in this function.

During a normal pregnancy, HCG secreted by the placenta maintains the corpus luteum after LH secretion decreases, supporting continued secretion of estrogen and progesterone, and preventing menstruation. HCG HAS NO KNOWN EFFECT ON FAT MOBILIZATION, APPETITE OR SENSE OF HUNGER, OR BODY FAT DISTRIBUTION.

INDICATIONS AND USAGE

HCG HAS NOT BEEN DEMONSTRATED TO BE EFFECTIVE ADJUNCTIVE THERAPY IN THE TREATMENT OF OBESITY. THERE IS NO SUBSTANTIAL EVIDENCE THAT IT INCREASES WEIGHT LOSS BEYOND THAT RESULTING FROM CALORIC RESTRICTION, THAT IT CAUSES A MORE ATTRACTIVE OR "NORMAL" DISTRIBUTION OF FAT, OR THAT IT DECREASES THE HUNGER AND DISCOMFORT ASSOCIATED WITH CALORIE-RESTRICTED DIETS.

1. Prepubertal cryptorchidism not due to anatomic obstruction. In general, HCG is thought to induce testicular descent in situations when descent would have occurred at puberty. HCG thus may help to predict whether or not orchiopexy will be needed in the future. Although, in some cases, descent following HCG administration is permanent, in most cases the response is temporary. Therapy is usually instituted between the ages of 4 and 9.
2. Selected cases of hypogonadotropic hypogonadism (hypogonadism secondary to a pituitary deficiency) in males.
3. Induction of ovulation and pregnancy in the anovulatory, infertile woman in whom the cause of anovulation is secondary and not due to primary ovarian failure, and who has been appropriately pretreated with human menotropins.

CONTRAINDICATIONS

Precocious puberty, prostatic carcinoma or other androgen-dependent neoplasm, prior allergic reaction to HCG. HCG may cause fetal harm when administered to a pregnant woman. Combined HCG/PMS (pregnant mare's serum) therapy has been noted to induce high incidences of external congenital anomalies in the offspring of mice, in a dose-dependent manner. The potential extrapolation to humans has not been determined.

WARNINGS

HCG should be used in conjunction with human menopausal gonadotropins only by physicians experienced with infertility problems who are familiar with the criteria for patient selection, contraindications, warnings, precautions, and adverse reactions described in the package insert for menotropins. The principal serious adverse reactions during this use are: (1) Ovarian hyperstimulation, a syndrome of sudden ovarian enlargement, ascites with or without pain, and/or pleural effusion; (2) Enlargement of preexisting ovarian cysts or rupture of ovarian cysts with resultant hemoperitoneum; (3) Multiple births, and (4) Arterial thromboembolism.

The recommended diluent for reconstitution is Bacteriostatic Water for Injection preserved with benzyl alcohol 0.9%. Benzyl alcohol has been reported to be associated with a fatal "Gasping Syndrome" in premature infants.

Anaphylaxis has been reported with urinary-derived HCG products.

PRECAUTIONS

General

1. Induction of androgen secretion by HCG may induce precocious puberty in patients treated for cryptorchidism. Therapy should be discontinued if signs of precocious puberty occur.
2. Since androgens may cause fluid retention, HCG should be used with caution in patients with cardiac or renal disease, epilepsy, migraine, or asthma.

Drug/Laboratory test

HCG can crossreact in the radioimmunoassay of gonadotropins, especially luteinizing hormone. Each individual laboratory should establish the degree of crossreactivity with their gonadotropin assay. Physicians should make the laboratory aware of patients on HCG if gonadotropin levels are requested.

Carcinogenesis, Mutagenesis, Impairment of Fertility

There have been sporadic reports of testicular tumors in otherwise healthy young men receiving HCG for secondary infertility. A causative relationship between HCG and tumor development in these men has not been established. Defects of forelimbs and of the central nervous system, as well as alterations in sex ratio, have been reported in mice on combined gonadotropin and HCG regimens. The dose of gonadotropin used was intended to induce superovulation. No mutagenic effect has been clearly established in humans. Fertility—see "INDICATIONS AND USAGE."

Pregnancy

See "CONTRAINDICATIONS" section. Combined HCG/PMS (pregnant mare's serum) therapy has been noted to induce high incidences of external congenital anomalies in the offspring of mice, in a dose-dependent manner. The potential extrapolation to humans has not been determined.

Nursing Mothers

It is not known whether this drug is excreted in human milk. Because many drugs are excreted in human milk, caution should be exercised when HCG is administered to a nursing woman.

Pediatric Use

Safety and effectiveness in children below the age of 4 have not been established.

ADVERSE REACTIONS

(see WARNINGS) Headache, irritability, restlessness, depression, fatigue, edema, precocious puberty, gynecomastia, pain at the site of injection. Hypersensitivity reactions both localized and systemic in nature, including erythema, urticaria, rash, angioedema, dyspnea and shortness of breath, have been reported. The relationship of these allergic-like events to the polypeptide hormone or the diluent containing benzyl alcohol is not clear.

DOSAGE AND ADMINISTRATION

(Intramuscular Use Only): The dosage regimen employed in any particular case will depend upon the indication for use, the age and weight of the patient, and the physician's preference. The following regimens have been advocated by various authorities.

Prepubertal cryptorchidism not due to anatomical obstruction:

- 4,000 USP Units three times weekly for three weeks.
- 5,000 USP Units every second day for four injections.
- 15 injections of 500 to 1,000 USP Units over a period of six weeks.
- 500 USP Units three times weekly for four to six weeks. If this course of treatment is not successful, another is begun one month later, giving 1,000 USP Units per injection.

Selected cases of hypogonadotropic hypogonadism in males:

- 500 to 1,000 USP Units three times a week for three weeks, followed by the same dose twice a week for three weeks.
- 4,000 USP Units three times weekly for six to nine months, following which the dosage may be reduced to 2,000 USP Units three times weekly for an additional three months.

Table 1. Final Concentration after Reconstitution
Reconstitution volume of bacteriostatic water for injection | 10,000 IU Vial Concentration | 5,000 IU Vial Concentration | Administration
1 mL | 10,000 IU/mL | 5,000 IU/mL | Administer entire dose at once
10 mL | 1,000 IU/mL | 500 IU/mL | Multiple dose administration, refrigerate between doses

NOTE: Prior to diluting NOVAREL with Bacteriostatic Water for Injection (Table 1):

- Remove the flip caps off the vial of bacteriostatic water and the vial of NOVAREL
- Wipe the tops of the vials with an alcohol pad or alcohol soaked gauze
- Do not touch the tops of the vials after you wipe them.

Induction of ovulation and pregnancy in the anovulatory, infertile woman in whom the cause of anovulation is secondary and not due to primary ovarian failure and who has been appropriately pretreated with human menotropins (See prescribing information for menotropins for dosage and administration for that drug product).

5,000 to 10,000 USP Units one day following the last dose of menotropins. (A dosage of 10,000 USP Units is recommended in the labeling for menotropins).

Parenteral drug products should be inspected visually for particulate matter and discoloration prior to administration, whenever solution and container permit.

Disposing of Needles and Syringes

To safely dispose of medical sharps, place used needles and syringes in a closeable, puncture-resistant container, such as a red biohazard sharps container. Sharps containers should then be taken to a collection center for proper disposal. Ask your physician or pharmacist or reference our website for more information about safely disposing used sharps.

In some states, it is illegal to throw away medical sharps in household garbage, recycling, and compost bins. Needles and other sharps must be placed in an approved sharps container and disposed of at an approved drop-off site.

HOW SUPPLIED

NOVAREL (chorionic gonadotropin) for Injection, USP, is available as individually packaged multiple-dose vials containing 5,000 or 10,000 USP Units per vial.

Each vial of NOVAREL is accompanied by a vial of sterile diluent containing 10 mL of Bacteriostatic Water for Injection, USP containing 0.9% benzyl alcohol.

NOVAREL is available in the following presentations:

- NDC 55566-1501-1: 10,000 USP units of chorionic gonadotropin injection in 1 vial with blue cap and 1 vial of diluent
- NDC 55566-1502-1: 5,000 USP units of chorionic gonadotropin injection in 1 vial with aqua cap and 1 vial of diluent

STORAGE AND HANDLING

Store at room temperature at 20° to 25°C (68° to 77°F), excursions permitted between 15° and 30°C (between 59° and 86°F) [See USP Controlled Room Temperature].

REFRIGERATE RECONSTITUTED PRODUCT AT 2° to 8°C (36° to 46°F) AND USE WITHIN 30 DAYS.

Manufactured by:
Ferring Pharmaceuticals Inc.
Parsippany, NJ 07054
U.S. License No. 2112

XXXXXXXXXX
Rev. 05/2023

PRINCIPAL DISPLAY PANEL - Kit Carton - 5,000 USP

NDC 55566-1502-1
Rx only

chorionic gonadotropin

Novarel®

for injection
5,000 USP units
for intramuscular use only

1 multiple-dose vial of Chorionic Gonadotropin
for Injection

1 multiple-dose vial of
Bacteriostatic Water
for injection, USP, 10 mL

FERRING
PHARMACEUTICALS